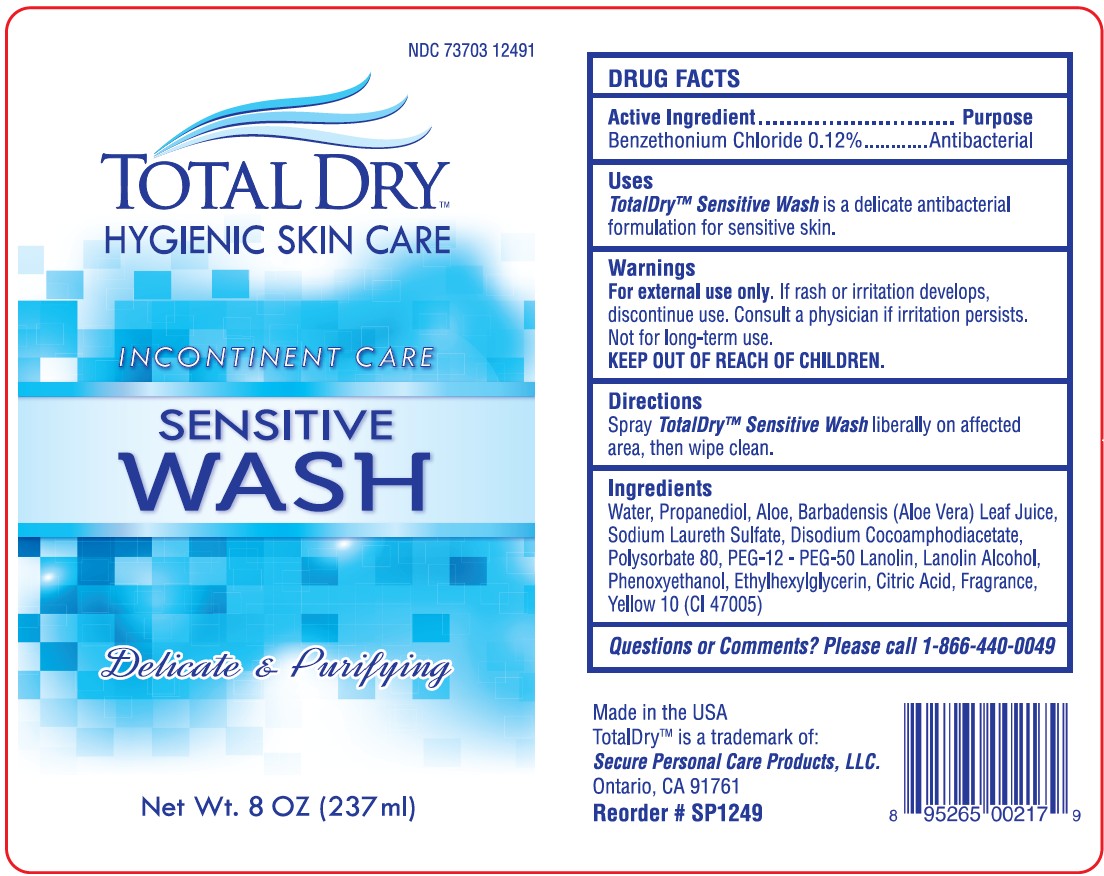 DRUG LABEL: TotalDry Sensitive Wash
NDC: 73703-124 | Form: SPRAY
Manufacturer: Secure Personal Care Products LLC
Category: otc | Type: HUMAN OTC DRUG LABEL
Date: 20250930

ACTIVE INGREDIENTS: BENZETHONIUM CHLORIDE 0.001212 g/1 mL
INACTIVE INGREDIENTS: WATER; PROPANEDIOL; ALOE; ALOE VERA LEAF; SODIUM LAURETH SULFATE; DISODIUM COCOAMPHODIACETATE; POLYSORBATE 80; PPG-12-PEG-50 LANOLIN; LANOLIN ALCOHOLS; PHENOXYETHANOL; ETHYLHEXYLGLYCERIN; CITRIC ACID MONOHYDRATE; D&C YELLOW NO. 10

SPC10-TotalDry™ Sensitive Wash

Active Ingredient

Benzethonium Chloride 0.12%

Purpose

Antibacterial

Uses

TotalDry™ Sensitive Washis a delicate antibacterial
formulation for sensitive skin.

Warnings

For external use only.If rash or irritation develops,
discontinue use. Consult a physician if irritation persists.
Not for long-term use.

KEEP OUT OF REACH OF CHILDREN

KEEP OUT OF REACH OF CHILDREN.

Directions

Spray TotalDry™ Sensitive Washliberally on affected
area, then wipe clean.

Ingredients

Water, Propanediol, Aloe, Barbadensis (Aloe Vera) Leaf Juice,
Sodium Laureth Sulfate, Disodium Cocoamphodiacetate,
Polysorbate 80, PEG-12 - PEG-50 Lanolin, Lanolin Alcohol,
Phenoxyethanol, Ethylhexylglycerin, Citric Acid, Fragrance,
Yellow 10 (CI 47005)

Questions or Comments?

Please call 1-866-440-0049